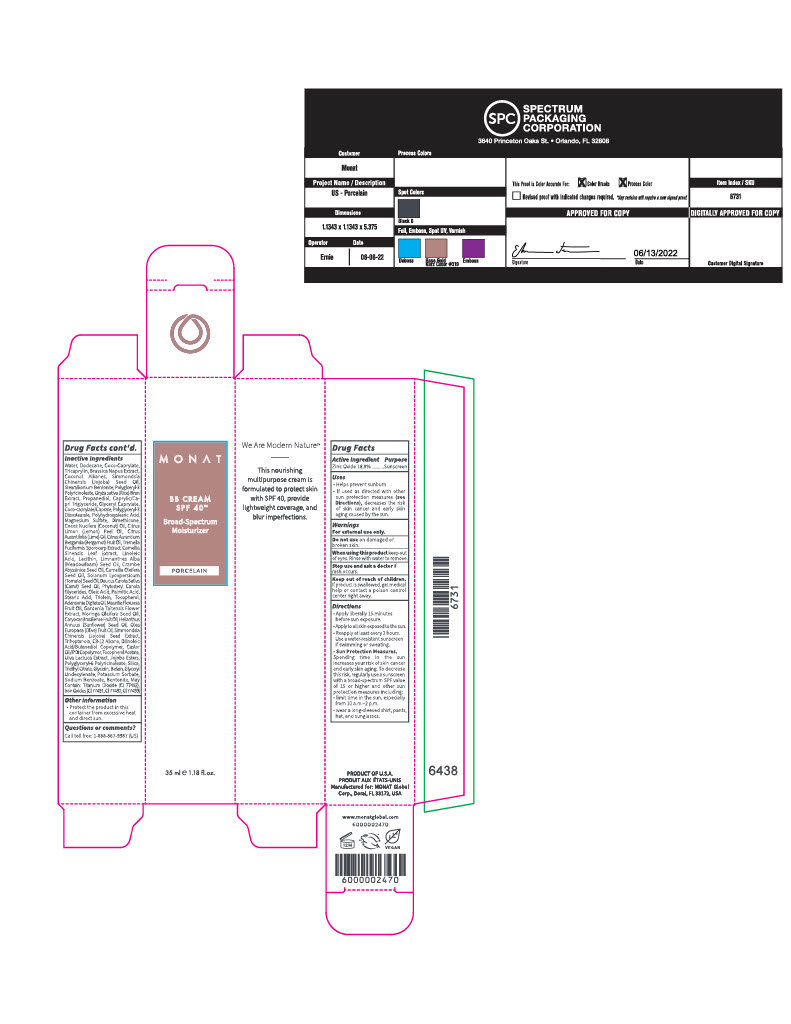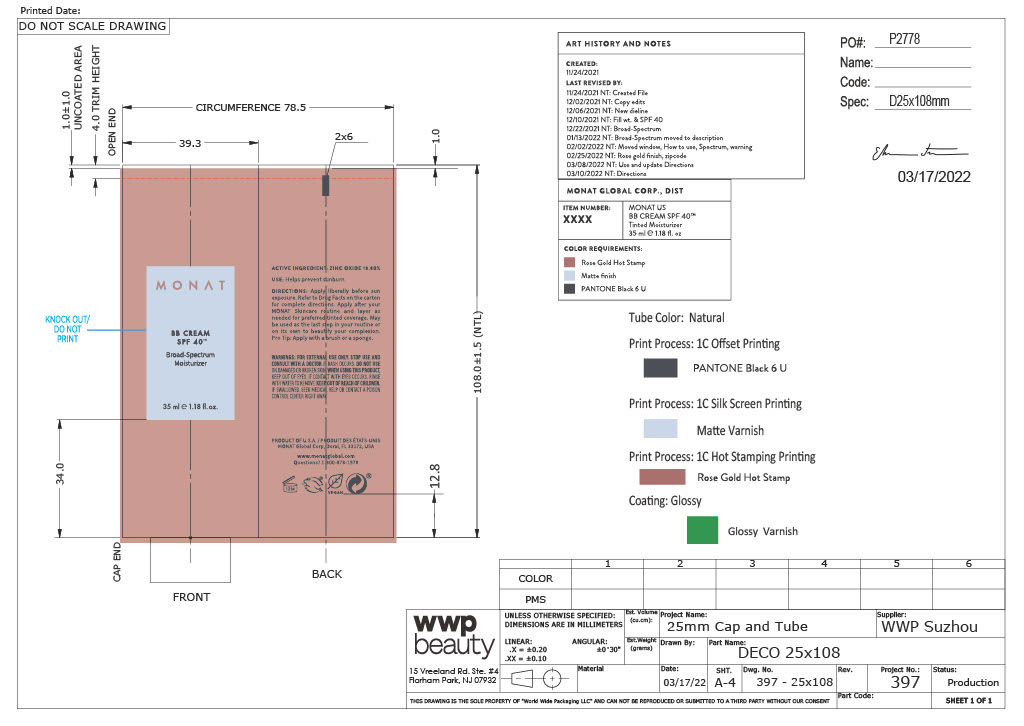 DRUG LABEL: Cream
NDC: 78518-007 | Form: CREAM
Manufacturer: MONAT GLOBAL CORP
Category: otc | Type: HUMAN OTC DRUG LABEL
Date: 20251226

ACTIVE INGREDIENTS: ZINC OXIDE 18.8 mg/100 mg
INACTIVE INGREDIENTS: CITRUS AURANTIIFOLIA FRUIT OIL; LINOLEIC ACID; LECITHIN, SUNFLOWER; LIMNANTHES ALBA WHOLE; CRAMBE HISPANICA SUBSP. ABYSSINICA SEED OIL; GLYCERYL CAPRYLATE; WATER; DODECANE; POLYGLYCERYL-3 DIISOSTEARATE; DIMETHICONE; COCOS NUCIFERA WHOLE; CITRUS LIMON SEED OIL; ALPHA-TOCOPHEROL ACETATE; HYDROLYZED JOJOBA ESTERS (POTASSIUM SALTS); COCO-CAPRYLATE; DILINOLEIC ACID/BUTANEDIOL COPOLYMER; ULVA LACTUCA; POLYGLYCERYL-6 POLYRICINOLEATE; SILICON DIOXIDE 0.111 mg/100 mg; CITRUS AURANTIUM FRUIT OIL; TREMELLA FUCIFORMIS WHOLE; CAMELLIA SINENSIS WHOLE; OLEIC ACID; STEARIC ACID; GLYCERYL TRIOLEATE; PHYTOSTERYL MACADAMIATE; TOCOPHEROL; CARYOCAR BRASILIENSE FRUIT OIL; TRIHEPTANOIN; SOLANUM LYCOPERSICUM; DAUCUS CAROTA SUBSP. SATIVUS SEED; MAURITIA FLEXUOSA FRUIT OIL; MORINGA OLEIFERA SEED OIL; HELIANTHUS ANNUUS WHOLE; OLEA EUROPAEA (OLIVE) OIL UNSAPONIFIABLES; BRASSICA NAPUS WHOLE; COCONUT ALKANES; POLYGLYCERYL-5 POLYRICINOLEATE; PROPANEDIOL; FERRIC OXIDE YELLOW; SIMMONDSIA CHINENSIS SEED; ORYZA SATIVA WHOLE; MEDIUM-CHAIN TRIGLYCERIDES; CAMELLIA OLEIFERA SEED; PALMITIC ACID; ADANSONIA DIGITATA SEED OIL; GARDENIA TAITENSIS FLOWER; CASTOR OIL; TRIETHYL CITRATE; GLYCERIN; GLYCERYL 1-UNDECYLENATE; SODIUM BENZOATE; BENTONITE; TITANIUM DIOXIDE; FERRIC OXIDE RED; FERROSOFERRIC OXIDE; COCO-CAPRYLATE/CAPRATE; POLYHYDROXYSTEARIC ACID (2300 MW); MAGNESIUM SULFATE, UNSPECIFIED FORM; BETAINE; POTASSIUM SORBATE; TRICAPRYLIN

BB Cream SPF 40 Broad-Spectrum Moisturizer (Porcelain)

Active Ingredient

Zinc Oxide 18.8%

Purpose

Sunscreen

Uses

- Helps prevent sunburn
- If used as directed with other sun protection measures (see Directions), decreases the risk of skin cancer and early skin aging caused by the sun.

WARNINGS

For external use only

Do not use on damage or broken skin

When using this product keep out of eyes. Rinse with water to remove.

Stop use and ask a doctor if rash occurs

Keep out of reach of children. If product is swallowed, get medical help or contact a poison control center right away.

Directions

- Apply liberally 15 minutes before sun exposure
- Apply to sll skin exposed to the sun
- Reapply at least every 2 hours
- Use a water resistant sunscreen if swimming or sweating
- Sun Protection Measures
  - Spending time in the sun increases your risk of skin cancer and early skin aging. To decrease this risk, regularly use a sunscreen with a broad-spectrum SPF value of 15 or higher and other sun protection measures including:
  - limit time in the sun, especially from 10am-2pm
  - wear a long-sleeved shirt, pants, hat, and sunglasses

Inactive Ingredients

Water/Eau, Dodecane, Coco-Caprylate, Tricaprylin, Brassica Napus Extract, Coconut Alkanes, Simmondsia Chinensis (Jojoba) Seed Oil, Stearalkonium Bentonite, Polyglceryl-3 Polyricinoleate, Oryza sativa (Rice) Bran Extract, Propanediol, Caprylic/Capric Triglyceride, Glyceryl Caprylate, Coco-caprylate/Caprate, Polyglyceryl-3 Diisostearate, Polyhydroxystearic Acid, Magnesium Sulfate, Dimethicone, Cocos Nucifera (Coconut) Oil, Citrus Limon (Lemon) Peel Oil, Citrus Aurantifolia (Lime) Oil, Citrus Aurantium Bergamia (Bergamot) Fruit Oil, Tremella Fuciformis Sporocarp Extract, Camellia Sinensis Leaf Extract, Linoleic Acid, Lecithin, Limnanthes Alba (Meadowfoam) Seed Oil, Crambe Abyssinica Seed Oil, Camellia Oleifera Seed Oil, Solanum Lycopersicum (Tomato) Seed Oil, Daucus Carota Sativa (Carrot) Seed Oil, Phytosteryl Canola Glycerides, Oleic Acid, Palmitic Acid, Stearic Acid, Triolein, Tocopherol, Adansonia Digitata Oil, Mauritia Flexuosa Fruit Oil, Gardenia Taitensis Flower Extract, Moringa Oleifera Seed Oil, Caryocar Brasiliense Fruit Oil, Helianthus Annuus (Sunflower) Seed Oil, Olea Europaea (Olive) Fruit Oil, Simmondsia Chinensis (Jojoba) Seed Extract, Triheptanoin, C9-12 Alkane, Dilinoleic Acid/Butanediol Copolymer, Castor Oil/IPDI Copolymer, Tocopherol Acetate, Ulva Lactuca Extract, Jojoba Esters, Polyglyceryl-6 Polyricinoleate, Silica, Triethyl Citrate, Glycerin, Betain, Glyceryl Undecylenate, Potassium Sorbate, Sodium Benzoate, Bentonite, May Contain: Titanium Dioxide (CI 77891), Iron Oxides (CI 77491, CI 77492, CI 77499).

Other information

- Protect the product in this container from excessive heat and direct sun.

Primary Package(Tube)

Tube

Outer Package(Carton)

Carton- Outer Package